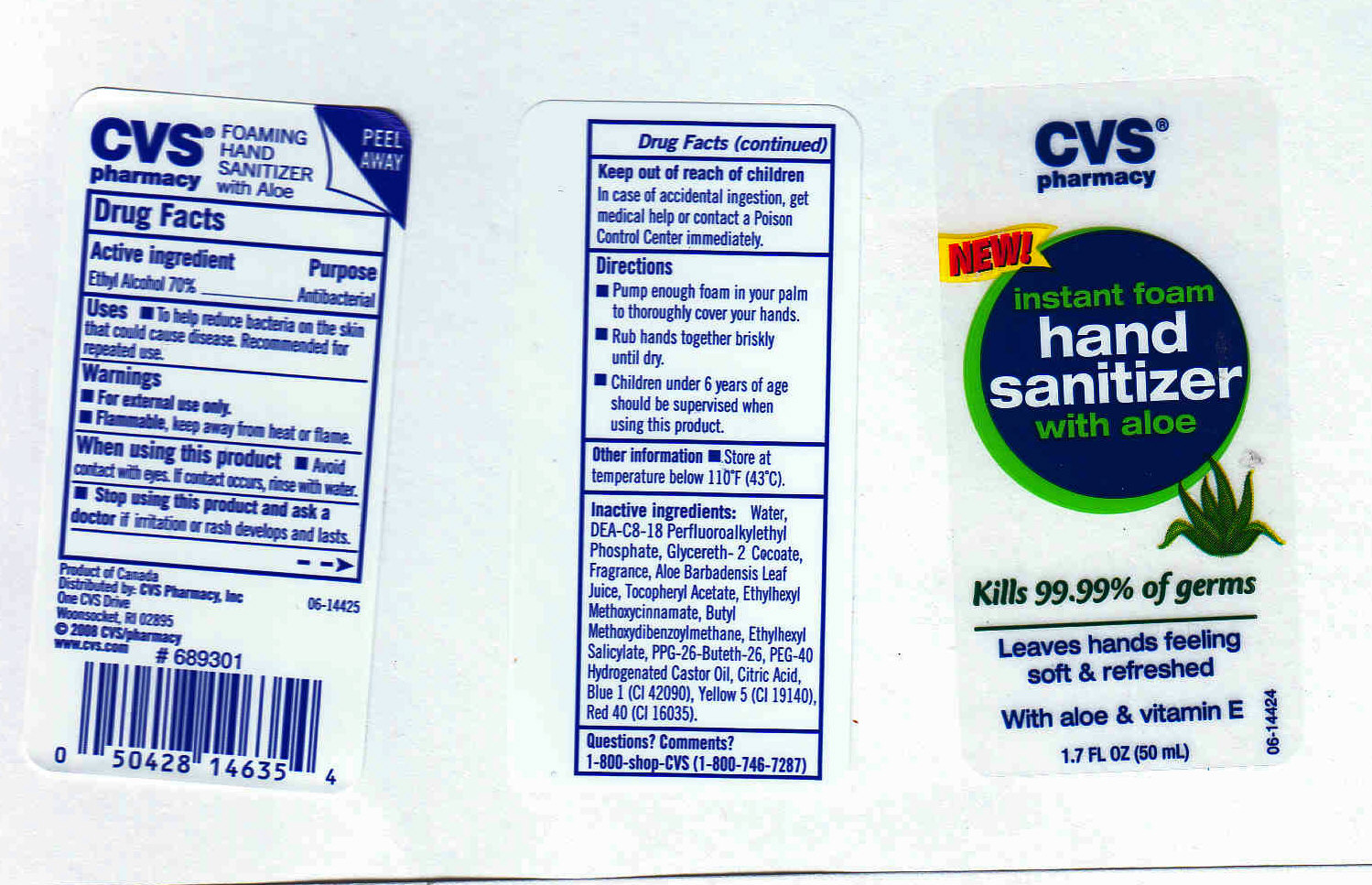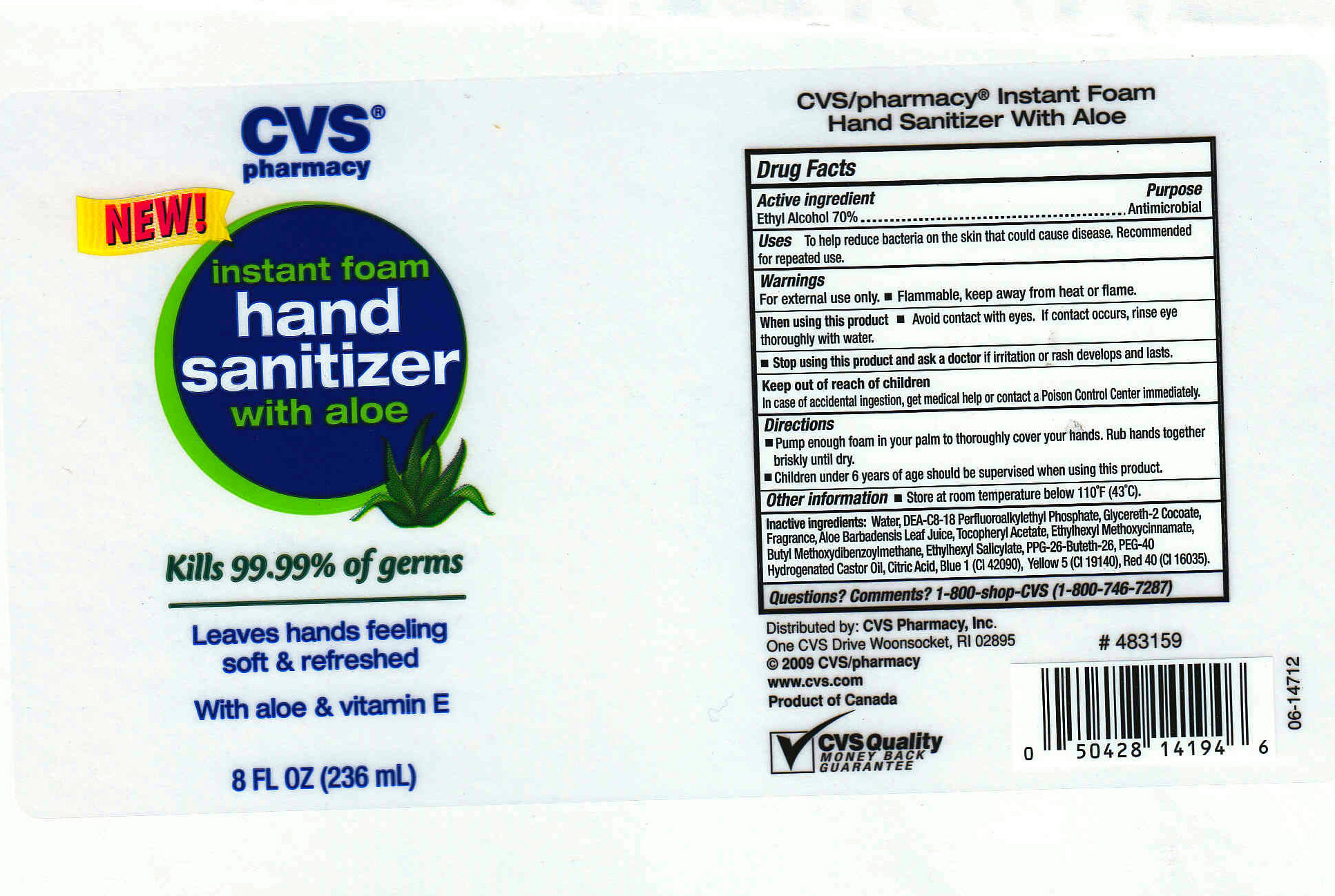 DRUG LABEL: CVS Pharmacy 
NDC: 63148-252 | Form: LIQUID
Manufacturer: Apollo Health and Beauty Care
Category: otc | Type: HUMAN OTC DRUG LABEL
Date: 20091217

ACTIVE INGREDIENTS: ALCOHOL 70 mL/100 mL
INACTIVE INGREDIENTS: WATER 28.8795 mL/100 mL; GLYCERETH-2 COCOATE 1.0 mL/100 mL; ALOE VERA LEAF 0.0001 mL/100 mL; .ALPHA.-TOCOPHEROL ACETATE, D- 0.0001 mL/100 mL; OCTISALATE 0.02 mL/100 mL; PROPYLENE OXIDE 0.02 mL/100 mL; FD&C BLUE NO. 1 0.0001 mL/100 mL; FD&C YELLOW NO. 5 0.0001 mL/100 mL; FD&C RED NO. 40 0.0001 mL/100 mL; OCTINOXATE 0.02 mL/100 mL; AVOBENZONE 0.02 mL/100 mL; POLYOXYL 40 HYDROGENATED CASTOR OIL 0.02 mL/100 mL; CITRIC ACID MONOHYDRATE 0.02 mL/100 mL

CVS Pharmacy Instant Foam Hand Sanitizer with Aloe

Active Ingredient

Ethyl Alcohol 70% (Antimicrobial)

Keep out of reach of children

In case of accidental ingestion, get medical help or contact a Poison Control Center immediately

Uses

To help reduce bacteria on the skin that could cause disease. Recommended for repeated use.

Questions? comments?

1-800-shop-CVS (1-800-746-7287)

Stop using this product and ask a doctor

if irritation or rash develops and lasts

When using this product

- Avoid contact with eyes. If contact occurs, rinse eye throughly with water.
- Pump enough foam in your palm to throughly cover your hands. Rub hands together briskly until dry.
- Children under 6 years of age should be supervised when using this product.

Warnings

- For external use only
- Flammable, keep away from heat or flame.

PACKAGE FRONT AND BACK LABELS

1. 8OZ (MM1) Labels8.jpg
2. 2OZ (MM2) Labels2.jpg